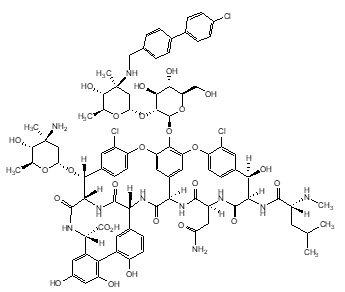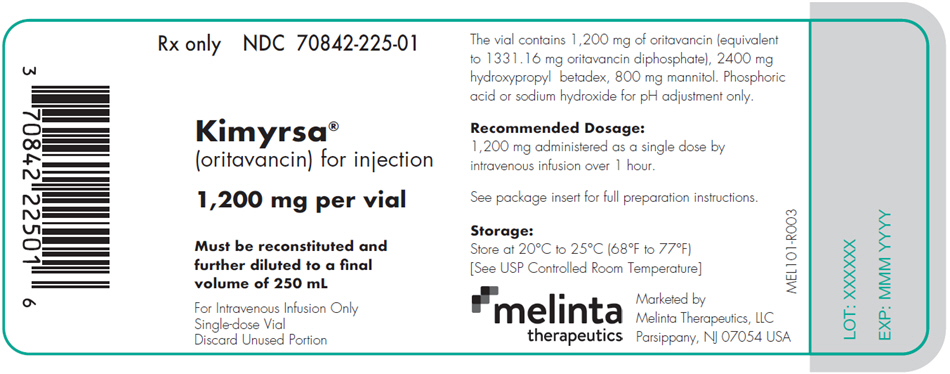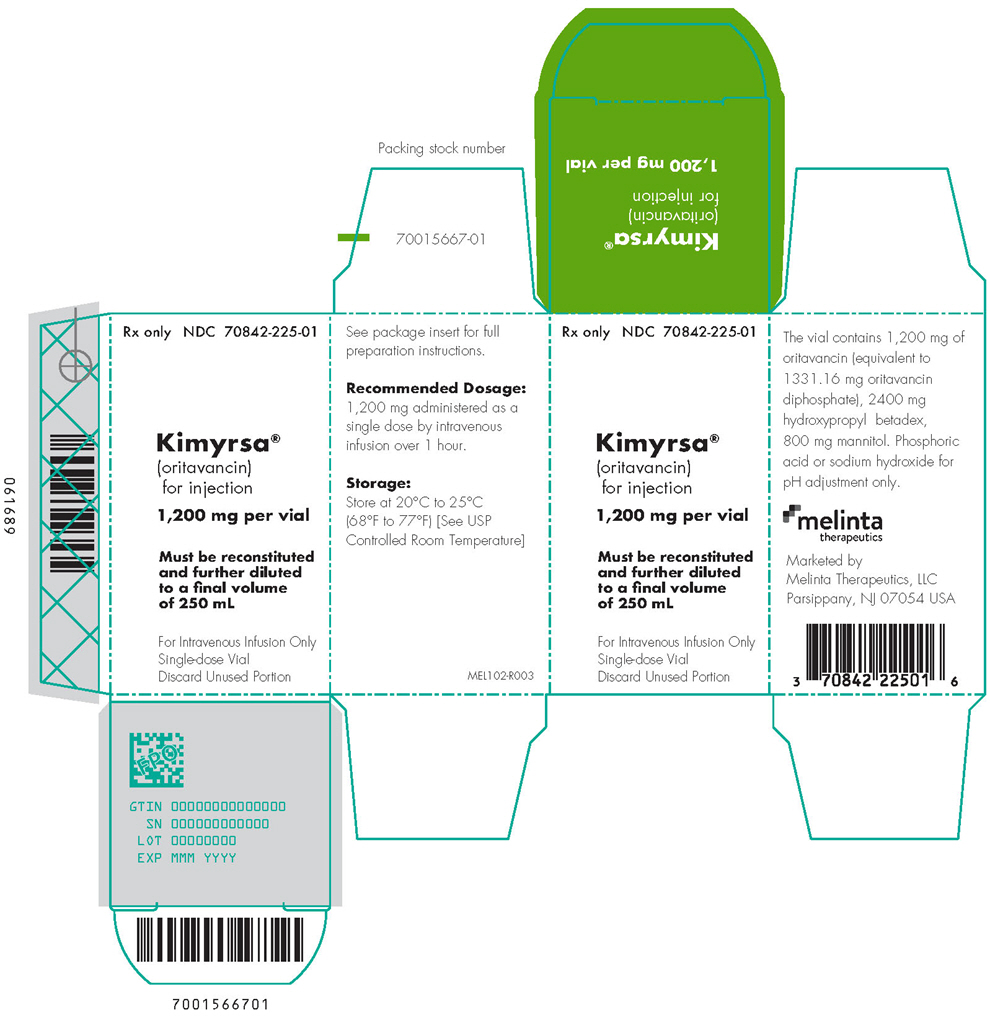 DRUG LABEL: Kimyrsa
NDC: 70842-225 | Form: INJECTION, POWDER, LYOPHILIZED, FOR SOLUTION
Manufacturer: Melinta Therapeutics, LLC
Category: prescription | Type: HUMAN PRESCRIPTION DRUG LABEL
Date: 20251218

ACTIVE INGREDIENTS: ORITAVANCIN DIPHOSPHATE 1200 mg/40 mL
INACTIVE INGREDIENTS: HYDROXYPROPYL BETADEX; MANNITOL; PHOSPHORIC ACID; SODIUM HYDROXIDE

HIGHLIGHTS OF PRESCRIBING INFORMATION

These highlights do not include all the information needed to use KIMYRSA safely and effectively. See full prescribing information for KIMYRSA.
KIMYRSA® (oritavancin) for injection, for intravenous use
Initial U.S. Approval: 2014

1 INDICATIONS AND USAGE

KIMYRSA is a lipoglycopeptide antibacterial drug indicated for the treatment of adult patients with acute bacterial skin and skin structure infections caused or suspected to be caused by susceptible isolates of designated Gram-positive microorganisms. (1.1)

To reduce the development of drug-resistant bacteria and maintain the effectiveness of KIMYRSA and other antibacterial drugs, KIMYRSA should be used only to treat or prevent infections that are proven or strongly suspected to be caused by bacteria. (1.2)

2 DOSAGE AND ADMINISTRATION

- There are two oritavancin products (KIMYRSA and ORBACTIV®, another oritavancin product) that have differences in dose strength, duration of infusion and preparation instructions, including reconstitution and dilution instructions and compatible diluents (2.1, 2.2, 2.3, 2.4)
- Administer 1,200 mg of KIMYRSA as a single dose by intravenous infusion over 1 hour. (2.1, 5.3)
- Carefully follow the recommended dosage and dose preparation instructions for KIMYRSA in the full prescribing information. (2.1, 2.2, 2.3)

3 DOSAGE FORMS AND STRENGTHS

For injection: 1,200 mg of lyophilized powder in a single-dose vial for reconstitution. (3)

4 CONTRAINDICATIONS

- Use of intravenous unfractionated heparin sodium is contraindicated for 120 hours (5 days) after KIMYRSA administration. (4.1, 5.1)
- Known hypersensitivity to oritavancin products. (4.2, 5.2)

5 WARNINGS AND PRECAUTIONS

- Coagulation test interference: Oritavancin has been shown to artificially prolong aPTT for up to 120 hours, and may prolong PT and INR for up to 12 hours and ACT for up to 24 hours. For patients who require aPTT monitoring within 120 hours of KIMYRSA dosing, consider a non-phospholipid dependent coagulation test such as a Factor Xa (chromogenic) assay or an alternative anticoagulant not requiring aPTT. (5.1, 7.2)
- Serious hypersensitivity reactions, including anaphylaxis, have been reported with the use of oritavancin products, including KIMYRSA. Discontinue infusion if signs of acute hypersensitivity occur. Carefully monitor patients with known hypersensitivity to glycopeptides. (5.2)
- Infusion Related Reactions: Infusion related reactions have been reported with the glycopeptide class of antimicrobial agents, including oritavancin products (e.g. KIMYRSA). Stopping or slowing the infusion may result in cessation of these reactions. (5.3)
- Clostridioides difficile-Associated Diarrhea: Evaluate patients if diarrhea occurs. (5.4)
- Concomitant warfarin use: Oritavancin has been shown to artificially prolong PT/INR for up to 12 hours (5.1). Patients should be monitored for bleeding if concomitantly receiving KIMYRSA and warfarin. (5.5)
- Osteomyelitis: Institute appropriate alternate antibacterial therapy in patients with confirmed or suspected osteomyelitis. (5.6)

6 ADVERSE REACTIONS

The most common adverse reactions (≥3%) in patients treated with oritavancin products were headache, nausea, vomiting, limb and subcutaneous abscesses, and diarrhea. The adverse reactions occurring in ≥2 patients receiving KIMYRSA were hypersensitivity, pruritus, chills and pyrexia. (6.1)

To report SUSPECTED ADVERSE REACTIONS, contact Melinta Therapeutics at 1-844-633-6568 or FDA at 1-800-FDA-1088 or www.fda.gov/medwatch.

FULL PRESCRIBING INFORMATION

1 INDICATIONS AND USAGE

1.1 Acute Bacterial Skin and Skin Structure Infections

KIMYRSA® is indicated for the treatment of adult patients with acute bacterial skin and skin structure infections (ABSSSI) caused by susceptible isolates of the following Gram-positive microorganisms:

Staphylococcus aureus (including methicillin-susceptible and methicillin-resistant isolates), Streptococcus pyogenes, Streptococcus agalactiae, Streptococcus dysgalactiae, Streptococcus anginosus group (includes S. anginosus, S. intermedius, and S. constellatus), and Enterococcus faecalis (vancomycin-susceptible isolates only).

1.2 Usage

To reduce the development of drug-resistant bacteria and maintain the effectiveness of KIMYRSA and other antibacterial drugs, KIMYRSA should be used only to treat or prevent infections that are proven or strongly suspected to be caused by susceptible bacteria. When culture and susceptibility information are available, they should be considered in selecting or modifying antibacterial therapy. In the absence of such data, local epidemiology and susceptibility patterns may contribute to the empiric selection of therapy.

2 DOSAGE AND ADMINISTRATION

2.1 Dosage and Administration Overview

There are two oritavancin products (KIMYRSA and ORBACTIV®, another oritavancin product) that:

- Are supplied in different dose strengths of oritavancin [see Dosage Forms and Strengths (3)].
- Have different recommended durations of infusion [see Dosage and Administration (2.2)].
- Have different preparation instructions, including differences in reconstitution, dilution, and compatible diluents [see Dosage and Administration (2.3, 2.4)].

Carefully follow the recommended dosage and dose preparation instructions for KIMYRSA in this prescribing information (PI) [see Dosage and Administration (2.1, 2.2, 2.3, 2.4)]. Refer to the ORBACTIV prescribing information for relevant information of the other oritavancin product.

2.2 Recommended Dosage

The recommended dosage of KIMYRSA is 1,200 mg administered as a single dose by intravenous infusion over 1 hour in patients 18 years and older [see Warnings and Precautions (5.3)].

2.3 Preparation of KIMYRSA for Intravenous Infusion

There are two oritavancin products (KIMYRSA and ORBACTIV, another oritavancin product) that have differences in dose strengths, duration of infusion, reconstitution and dilution instructions, and compatible diluents. Carefully follow the reconstitution, and dilution instructions with the appropriate compatible diluent for KIMYRSA specified in this prescribing information. Refer to the ORBACTIV prescribing information for relevant information of the other oritavancin product.

KIMYRSA is intended for intravenous infusion, only after reconstitution and dilution.

One KIMYRSA 1,200 mg single-dose vial needs to be reconstituted and diluted to prepare a single 1,200 mg intravenous dose.

Reconstitution: Aseptic technique should be used to reconstitute one KIMYRSA 1,200 mg vial.

- Add 40 mL of sterile water for injection (SWFI) to reconstitute the vial to provide a 30 mg/mL solution.
- Gently swirl the contents to avoid foaming and ensure that all KIMYRSA powder is completely dissolved to form a reconstituted solution.
- Parenteral drug products should be inspected visually for particulate matter and discoloration prior to administration, whenever solution and container permit. The reconstituted vial should appear to be a clear, colorless to pink solution, free of visible particles.

Dilution: Use 0.9% sodium chloride injection or 5% dextrose in sterile water (D5W) for dilution to prepare the final intravenous solution for infusion. Since no preservative or bacteriostatic agent is present in KIMYRSA, aseptic technique must be used in preparing the final intravenous solution as follows:

- Withdraw and discard 40 mL from a 250 mL intravenous bag of 0.9% sodium chloride injection or D5W.
- Withdraw 40 mL of the reconstituted vial of KIMYRSA and add to the intravenous bag of 0.9% sodium chloride injection or D5W to bring the bag volume to 250 mL. This yields a concentration of 4.8 mg/mL.

Discard any unused portion of the reconstituted solution remaining in the vial.

Storage and Use of Intravenous Solution: Diluted intravenous solution in an infusion bag should be used within 4 hours when stored at room temperature, or used within 12 hours when refrigerated at 2 to 8°C (36 to 46°F). The combined storage time (reconstituted solution in the vial and diluted solution in the bag) and 1 hour infusion time should not exceed 4 hours at room temperature or 12 hours if refrigerated.

2.4 Compatibilities

KIMYRSA solution for administration by 1-hour infusion is compatible with:

- 0.9% sodium chloride injection
- 5% dextrose in sterile water (D5W)

2.5 Incompatibilities

Drugs formulated at a basic or neutral pH may be incompatible with KIMYRSA. KIMYRSA should not be administered simultaneously with commonly used intravenous drugs through a common intravenous port. If the same intravenous line is used for sequential infusion of additional medications, the line should be flushed before and after infusion of KIMYRSA with 0.9% sodium chloride injection or D5W.

3 DOSAGE FORMS AND STRENGTHS

KIMYRSA is supplied as sterile, white to off-white or pink lyophilized powder containing 1,200 mg of oritavancin (as oritavancin diphosphate) in a single-dose clear glass vial, which must be reconstituted and further diluted prior to intravenous administration.

4 CONTRAINDICATIONS

4.1 Intravenous Unfractionated Heparin Sodium

Use of intravenous unfractionated heparin sodium is contraindicated for 120 hours (5 days) after KIMYRSA administration because the activated partial thromboplastin time (aPTT) test results may remain falsely elevated for up to 120 hours (5 days) after KIMYRSA administration [see Warnings and Precautions (5.1) and Drug Interactions (7.2)].

4.2 Hypersensitivity

KIMYRSA is contraindicated in patients with known hypersensitivity to oritavancin products.

5 WARNINGS AND PRECAUTIONS

5.1 Coagulation Test Interference

Oritavancin has been shown to artificially prolong aPTT for up to 120 hours, PT and INR for up to 12 hours, and activated clotting time (ACT) for up to 24 hours following administration of a single 1,200 mg dose by binding to and preventing action of the phospholipid reagents commonly used in laboratory coagulation tests. Oritavancin has also been shown to elevate D-dimer concentrations up to 72 hours after oritavancin administration.

For patients who require aPTT monitoring within 120 hours of KIMYRSA dosing, a non-phospholipid dependent coagulation test such as a Factor Xa (chromogenic) assay or an alternative anticoagulant not requiring aPTT monitoring may be considered [see Contraindications (4.1) and Drug Interactions (7.2)].

Oritavancin has no effect on the coagulation system in vivo.

5.2 Hypersensitivity

Serious hypersensitivity reactions, including anaphylaxis, have been reported with the use of oritavancin products, including KIMYRSA. If an acute hypersensitivity reaction occurs during KIMYRSA infusion, discontinue KIMYRSA immediately and institute appropriate supportive care. Before using KIMYRSA, inquire carefully about previous hypersensitivity reactions to glycopeptides. Due to the possibility of cross-sensitivity, carefully monitor for signs of hypersensitivity during KIMYRSA infusion in patients with a history of glycopeptide allergy. In the Phase 3 ABSSSI clinical trials, the median onset of hypersensitivity reactions in oritavancin-treated patients was 1.2 days and the median duration of these reactions was 2.4 days [see Adverse Reactions (6.1)].

5.3 Infusion Related Reactions

Infusion related reactions have been reported with the glycopeptide class of antimicrobial agents, including oritavancin products (e.g. KIMYRSA), including flushing of the upper body, urticaria, pruritus and/or rash [see Adverse Reactions (6.1)]. Infusion reactions characterized by chest pain, back pain, chills and tremor have been observed with the use of oritavancin, including after the administration of more than one dose of oritavancin during a single course of therapy.

Stopping or slowing the infusion may result in cessation of these reactions. The safety and effectiveness of more than one dose of KIMYRSA during a single course of therapy have not been established [see Dosage and Administration (2.2)].

5.4 Clostridioides difficile-Associated Diarrhea

Clostridioides difficile-associated diarrhea (CDAD) has been reported for nearly all systemic antibacterial drugs, including oritavancin products (e.g. KIMYRSA), and may range in severity from mild diarrhea to fatal colitis. Treatment with antibacterial agents alters the normal flora of the colon and may permit overgrowth of C. difficile.

C. difficile produces toxins A and B which contribute to the development of CDAD. Hypertoxin-producing strains of C. difficile cause increased morbidity and mortality, as these infections can be refractory to antibacterial therapy and may require colectomy. CDAD must be considered in all patients who present with diarrhea following antibacterial use. Careful medical history is necessary because CDAD has been reported to occur more than 2 months after the administration of antibacterial agents.

If CDAD is suspected or confirmed, antibacterial use not directed against C. difficile may need to be discontinued. Appropriate fluid and electrolyte management, protein supplementation, antibacterial treatment of C. difficile, and surgical evaluation should be instituted as clinically indicated.

5.5 Potential Risk of Bleeding with Concomitant Use of Warfarin

Oritavancin has been shown to artificially prolong prothrombin time (PT) and international normalized ratio (INR) for up to 12 hours, making the monitoring of the anticoagulation effect of warfarin unreliable up to 12 hours after an oritavancin dose [see Warnings and Precautions (5.1)].

Patients should be monitored for bleeding if concomitantly receiving KIMYRSA and warfarin [see Drug Interactions (7.1)].

5.6 Osteomyelitis

In Phase 3 ABSSSI clinical trials, more cases of osteomyelitis were reported in the oritavancin treated arm than in the vancomycin-treated arm. Monitor patients treated with KIMYRSA for signs and symptoms of osteomyelitis. If osteomyelitis is suspected or diagnosed, institute appropriate alternate antibacterial therapy [see Adverse Reactions (6.1)].

5.7 Development of Drug Resistant Bacteria

Prescribing KIMYRSA in the absence of a proven or strongly suspected bacterial infection or a prophylactic indication is unlikely to provide benefit to the patient and increases the risk of the development of drug-resistant bacteria [see Patient Counseling Information (17)].

6 ADVERSE REACTIONS

The following adverse reactions are also discussed in the Warnings and Precautions section of labeling:

Hypersensitivity Reactions [see Warnings and Precautions (5.2)]

Infusion Related Reactions [see Warnings and Precautions (5.3)]

Clostridioides difficile-Associated Diarrhea [see Warnings and Precautions (5.4)]

Osteomyelitis [see Warnings and Precautions (5.6)]

6.1 Clinical Trials Experience

Because clinical trials are conducted under widely varying conditions, adverse reaction rates observed in the clinical trials of oritavancin products cannot be directly compared to rates in the clinical trials of another drug and may not reflect the rates observed in practice.

The safety of KIMYRSA has been established from adequate and well-controlled trials of another oritavancin product, ORBACTIV (hereinafter referred to as oritavancin), in patients with ABSSSI, and a study of KIMYRSA in patients with ABSSSI.

Oritavancin has been evaluated in two, double-blind, controlled ABSSSI clinical trials, which included 976 adult patients treated with a single 1,200 mg intravenous dose of oritavancin and 983 patients treated with intravenous vancomycin for 7 to 10 days. The median age of patients treated with oritavancin was 45.6 years, ranging between 18 and 89 years of age with 8.8% ≥65 years of age. Patients treated with oritavancin were predominantly male (65.4%), 64.4% were Caucasian, 5.8% were African American, and 28.1% were Asian. Safety was evaluated for up to 60 days after dosing.

In the pooled ABSSSI clinical trials, serious adverse reactions were reported in 57/976 (5.8%) patients treated with oritavancin and 58/983 (5.9%) treated with vancomycin. The most commonly reported serious adverse reaction was cellulitis in both treatment groups: 11/976 (1.1%) in oritavancin and 12/983 (1.2%) in the vancomycin arms, respectively.

The most commonly reported adverse reactions (≥3%) in patients receiving a single 1,200 mg dose of oritavancin in the pooled ABSSSI clinical trials were: headache, nausea, vomiting, limb and subcutaneous abscesses, and diarrhea.

In the pooled ABSSSI clinical trials, oritavancin was discontinued due to adverse reactions in 36/976 (3.7%) of patients; the most common reported reactions leading to discontinuation were cellulitis (4/976, 0.4%) and osteomyelitis (3/976, 0.3%).

Table 1 provides selected adverse reactions occurring in ≥1.5% of patients receiving oritavancin in the pooled ABSSSI clinical trials. There were 540 (55.3%) patients in the oritavancin arm and 559 (56.9%) patients in the vancomycin arm, who reported ≥1 adverse reaction.

Table 1: Incidence of Selected Adverse Reactions Occurring in ≥1.5% of Patients Receiving Oritavancin in the Pooled ABSSSI Clinical Trials
Adverse Reactions | Oritavancin N=976 (%) | Vancomycin N=983 (%)
Gastrointestinal disorders
Diarrhea | 36 (3.7) | 32 (3.4)
Nausea | 97 (9.9) | 103 (10.5)
Vomiting | 45 (4.6) | 46 (4.7)
Nervous system disorders
Dizziness | 26 (2.7) | 26 (2.6)
Headache | 69 (7.1) | 66 (6.7)
General disorders and administration
Infusion site phlebitis | 24 (2.5) | 15 (1.5)
Infusion site reaction | 19 (1.9) | 34 (3.5)
Infections and infestations
Abscess (limb and subcutaneous) | 37 (3.8) | 23 (2.3)
Investigations
Alanine aminotransferase increased | 27 (2.8) | 15 (1.5)
Aspartate aminotransferase increased | 18 (1.8) | 15 (1.5)
Cardiac disorders
Tachycardia | 24 (2.5) | 11 (1.1)

The following selected adverse reactions were reported in oritavancin-treated patients at a rate of less than 1.5%:

Blood and lymphatic system disorders: anemia, eosinophilia

General disorders and administration site conditions: infusion site erythema, extravasation, induration, pruritus, rash, edema peripheral

Immune system disorders: hypersensitivity

Infections and infestations: osteomyelitis

Investigations: total bilirubin increased, hyperuricemia

Metabolism and nutrition disorders: hypoglycemia

Musculoskeletal and connective tissue disorders: tenosynovitis, myalgia

Respiratory, thoracic and mediastinal disorders: bronchospasm, wheezing

Skin and subcutaneous tissue disorders: urticaria, angioedema, erythema multiforme, pruritus, leucocytoclastic vasculitis, rash.

KIMYRSA has been evaluated in a randomized, open-label, multi-center ABSSSI study which included 50 adult patients treated with a single 1,200 mg intravenous dose of KIMYRSA administered by intravenous infusion over 1 hour, and 52 patients treated with a single 1,200 mg intravenous dose of oritavancin administered by intravenous infusion over 3 hours.

Selected adverse reactions occurring in ≥2 patients receiving either KIMYRSA or oritavancin in the open-label, multi-center ABSSSI study were diarrhea, nausea, vomiting, hypersensitivity, pruritus, chills, headache and pyrexia.

7 DRUG INTERACTIONS

7.1 Effect of KIMYRSA on CYP Substrates

A screening drug-drug interaction study indicated that oritavancin is a nonspecific, weak inhibitor (CYP2C9 and CYP2C19) or inducer (CYP3A4 and CYP2D6) of several CYP isoforms [see Clinical Pharmacology (12.3)]. A drug-drug interaction study that assessed the interaction potential of a single 1,200 mg dose of oritavancin on the pharmacokinetics of S-warfarin (CYP2C9 probe substrate) showed no effect of oritavancin on S-warfarin Cmax or AUC.

Avoid administering KIMYRSA concomitantly with drugs that are predominantly metabolized by one of the affected CYP450 enzymes, as co-administration may increase or decrease concentrations of those drugs. Patients should be closely monitored for signs of toxicity or lack of efficacy if they have been given KIMYRSA while on a potentially affected compound (e.g., patients should be monitored for bleeding if concomitantly receiving KIMYRSA and warfarin).

7.2 Drug-Laboratory Test Interactions

Prolongation of Certain Laboratory Coagulation Tests

KIMYRSA may artificially prolong certain laboratory coagulation tests (see Table 2) by binding to and preventing the action of the phospholipid reagents which activate coagulation in commonly used laboratory coagulation tests [see Contraindications (4.1) and Warnings and Precautions (5.1, 5.5)]. For patients who require monitoring of anticoagulation effect within the indicated time after KIMYRSA dosing, a non-phospholipid dependent coagulation test such as a Factor Xa (chromogenic) assay or an alternative anticoagulant not requiring aPTT monitoring may be considered.

Oritavancin does not interfere with coagulation in vivo. In addition, oritavancin does not affect tests that are used for diagnosis of Heparin Induced Thrombocytopenia (HIT).

Table 2: Coagulation Tests Affected and Unaffected by Oritavancin
Elevated by Oritavancin | Unaffected by Oritavancin
Prothrombin time (PT) up to 12 hours | Chromogenic Factor Xa Assay
International normalized ratio (INR) up to 12 hours | Thrombin Time (TT)
Activated partial thromboplastin time (aPTT) up to 120 hours
Activated clotting time (ACT) up to 24 hours
Silica clot time (SCT) up to 18 hours
Dilute Russell's viper venom time (DRVVT) up to 72 hours
D-dimer up to 72 hours

Positive Indirect and Direct Antiglobulin Tests (IAT/DAT)

Positive IAT/DAT were noted with administration of oritavancin products, including KIMYRSA, in studies with healthy volunteers and patients with ABSSSI. Positive IAT may interfere with cross-matching before blood transfusion [see Clinical Pharmacology (12.6)].

8 USE IN SPECIFIC POPULATIONS

8.1 Pregnancy

Risk Summary

There are no available data on KIMYRSA use in pregnant women to evaluate for a drug- associated risk of major birth defects, miscarriage or adverse maternal or fetal outcomes. In animal reproduction studies, no effects on embryo-fetal development or survival were observed in pregnant rats or rabbits treated at the highest doses throughout organogenesis with intravenous oritavancin, at doses equivalent to 25% of the single clinical dose of 1,200 mg (see Data).

The estimated background risk of major birth defects and miscarriage for the indicated population is unknown. All pregnancies have a background risk of birth defect, loss, or other adverse outcomes. In the U.S. general population, the estimated background risk of major birth defects and miscarriage in clinically recognized pregnancies is 2% to 4% and 15% to 20%, respectively.

Data

Animal Data

Reproduction studies performed in rats and rabbits have revealed no evidence of harm to the fetus due to oritavancin at the highest doses administered throughout organogenesis, 30 mg/kg/day (gestation days 6-17) and 15 mg/kg/day (gestation days 7-19), respectively. Those doses would be equivalent to a human dose of 300 mg, or 25% of the single clinical dose of 1,200 mg. Higher doses were not evaluated in nonclinical developmental and reproductive toxicology studies.

8.2 Lactation

Risk Summary

There are no data on the presence of oritavancin in human milk, the effects on the breastfed- child, or the effects on milk production. Oritavancin is present in the breast milk of rats (see Data). When a drug is present in animal milk, it is likely that the drug will be present in human milk.

The developmental and health benefits of breastfeeding should be considered along with the mother's clinical need for KIMYRSA and any potential adverse effects on the breast-fed child from KIMYRSA or from the underlying maternal condition.

Data

Following a single intravenous infusion in lactating rats, radio-labeled [^14C]-oritavancin was excreted in milk and absorbed by nursing pups.

8.4 Pediatric Use

Safety and effectiveness of KIMYRSA in pediatric patients (younger than 18 years of age) have not been established.

8.5 Geriatric Use

The pooled Phase 3 ABSSSI clinical trials of oritavancin did not include sufficient numbers of subjects aged 65 and older to determine whether they respond differently from younger subjects. Other reported clinical experience has not identified differences in responses between the elderly and younger patients, but greater sensitivity of some older individuals cannot be ruled out.

8.6 Renal Impairment

No dosage adjustment of KIMYRSA is needed in patients with mild or moderate renal impairment [see Clinical Pharmacology (12.3)]. The pharmacokinetics of KIMYRSA in severe renal impairment have not been evaluated. Oritavancin is not removed from blood by hemodialysis.

8.7 Hepatic Impairment

No dosage adjustment of KIMYRSA is needed in patients with mild or moderate hepatic impairment. The pharmacokinetics of KIMYRSA in patients with severe hepatic insufficiency has not been studied [see Dosage and Administration (2.2), Clinical Pharmacology (12.3)].

10 OVERDOSAGE

Based on an in vitro hemodialysis study, KIMYRSA is unlikely to be removed from blood by hemodialysis. In the event of overdose, supportive measures should be taken.

11 DESCRIPTION

KIMYRSA (oritavancin) for injection contains oritavancin diphosphate, a semisynthetic lipoglycopeptide antibacterial drug for intravenous infusion.

The chemical name for oritavancin is [4"R]-22-O-(3-amino-2,3,6-trideoxy-3-C-methyl-α-L-arabino-hexopyranosyl)-N3''-[(4'-chloro[1,1'-biphenyl]-4-yl)methyl] vancomycin phosphate [1:2] [salt]. The empirical formula of oritavancin diphosphate is C86H97N10O26Cl3•2H3PO4 and the molecular weight is 1989.09. The chemical structure is represented below:

∙2H3PO4

KIMYRSA for injection is supplied as a sterile white to off-white or pink lyophilized powder in a single-dose clear glass vial that contains 1,200 mg of oritavancin (equivalent to 1331.16 mg oritavancin diphosphate) and the following inactive ingredients: hydroxypropyl-β-cyclodextrin (HPβCD) (2400 mg), mannitol (800 mg) and phosphoric acid or sodium hydroxide (to adjust pH 4.0 to 6.0).

The vial is reconstituted with sterile water for injection and further diluted with 0.9% sodium chloride injection or 5% dextrose in sterile water (D5W) for intravenous infusion. Both the reconstituted solution and the diluted solution for infusion should be a clear, colorless to pink solution, free of visible particles [see Dosage and Administration (2.3)].

12 CLINICAL PHARMACOLOGY

12.1 Mechanism of Action

Oritavancin is an antibacterial drug [see Microbiology (12.4)].

12.2 Pharmacodynamics

The antimicrobial activity of oritavancin appears to correlate with the ratio of area under the concentration-time curve to minimal inhibitory concentration (AUC/MIC) based on animal models of infection. The AUC from time zero to 72 hours correlates with antimicrobial activity in both preclinical and clinical studies.

Exposure-response analyses from both preclinical and clinical studies support the treatment of clinically relevant gram-positive microorganisms (e.g. S. aureus and S. pyogenes) causative of ABSSSI with a single 1,200 mg dose of oritavancin.

Cardiac Electrophysiology

In a thorough QTc study of 135 healthy subjects at a dose 1.3 times the 1,200 mg recommended dose, oritavancin did not prolong the QTc interval to any clinically relevant extent.

12.3 Pharmacokinetics

The mean (±SD) pharmacokinetic parameters of oritavancin products (KIMYRSA and oritavancin) in patients with ABSSSI are presented in Table 3.

Table 3: Mean (±SD) Pharmacokinetic Parameters following a single 1,200 mg dose of KIMYRSA by intravenous infusion over 1 hour (N= 50) and Oritavancin by intravenous infusion over 3 hours (N=50) in Patients with ABSSSI
Pharmacokinetic Parameter | KIMYRSA (1 hour) Mean (± SD) | Oritavancin (3 hour) Mean (± SD)
Cmax (µg/mL) | 148 (±43.0) | 112 (±34.5)
AUC0-72 (h∙µg /mL) | 1460 (±511) | 1470 (±582)
Cmax, Maximum plasma concentration; AUC0-72, Area under the plasma concentration-time curve from time zero to 72 hours; SD, Standard deviation.

Oritavancin exhibits linear pharmacokinetics at a dose up to 1,200 mg. The mean, population-predicted oritavancin concentration-time profile displays a multi-exponential decline with a long terminal plasma half-life.

Distribution

Oritavancin is approximately 85% bound to human plasma proteins.

Based on population pharmacokinetic (PK) analysis, the population mean total volume of distribution is estimated to be approximately 87.6 L, indicating that oritavancin is extensively distributed into the tissues.

Exposures of oritavancin in skin blister fluid were approximately 20% of those in plasma (AUC0-24) after single 800 mg dose in healthy subjects.

Metabolism/Excretion

Non-clinical studies, including in vitro human liver microsome studies, indicated that oritavancin is not metabolized. No mass balance study has been conducted in humans. In humans, oritavancin is slowly excreted unchanged in feces and urine, with less than 1% and 5% of the dose recovered in feces and urine, respectively, after 2 weeks of collection.

Oritavancin has a terminal half-life of approximately 245 hours and a clearance of 0.445 L/h, based on population PK analyses.

Specific Populations

No dosage adjustments of KIMYRSA are required for patients with mild-to-moderate renal or mild-to-moderate hepatic impairment or other subpopulations, including age, gender, race, and weight.

Renal Impairment

The PK of oritavancin was examined in the Phase 3 ABSSSI trials in patients with normal renal function, CrCL ≥80 mL/min (n=238), mild renal impairment, CrCL 50-79 mL/min (n=48), and moderate renal impairment, CrCL 30-49 mL/min (n=11). Population PK analysis indicated that mild-to-moderate renal impairment had no clinically relevant effect on the exposure of oritavancin. No dedicated studies in dialysis patients have been conducted.

The solubilizer HPβCD is excreted in urine. Clearance of HPβCD may be reduced in patients with renal impairment. The clinical significance of this finding is unknown.

Dosage adjustment of KIMYRSA is not needed in patients with mild or moderate renal impairment. The PK of oritavancin in patients with severe renal impairment have not been evaluated.

Hepatic Impairment

The PK of oritavancin was evaluated in study of subjects with moderate hepatic impairment (Child-Pugh Class B) (n=20) and compared with healthy subjects (n=20) matched for gender, age, and weight. There were no relevant changes in PK of oritavancin in subjects with moderate hepatic impairment.

Dosage adjustment of KIMYRSA is not needed in patients with mild or moderate hepatic impairment. The PK of oritavancin in patients with severe hepatic insufficiency has not been studied.

Age, Gender, Weight and Race

Population PK analysis from the Phase 3 ABSSSI trials in patients indicated that gender, age, weight, and race had no clinically relevant effect on the exposure of oritavancin. No dosage adjustment of KIMYRSA is warranted in these subpopulations.

Drug Interactions

In vitro studies with human liver microsomes showed that oritavancin inhibited the activities of cytochrome P450 (CYP) enzymes 1A2, 2B6, 2D6, 2C9, 2C19, and 3A4. The observed inhibition of multiple CYP isoforms by oritavancin in vitro is likely to be reversible and noncompetitive. In vitro studies indicate that oritavancin is neither a substrate nor an inhibitor of the efflux transporter P-glycoprotein (P-gp).

Drugs that Inhibit or Induce CYP450 Enzymes

A screening drug-drug interaction study was conducted in healthy volunteers (n=16) evaluating the concomitant administration of a single 1,200 mg dose of oritavancin with probe substrates for several CYP450 enzymes. The results showed that oritavancin is a weak inducer of CYP3A4 (a decrease of 18% in the mean AUC of midazolam) and CYP2D6 (decrease of 31% in the ratio of dextromethorphan to dextrorphan concentrations in the urine after administration of dextromethorphan). Oritavancin was also a weak inhibitor of CYP2C19 (increase of 15% in the ratio of omeprazole to 5-OH-omeprazole concentrations in the plasma after administration of omeprazole) and CYP2C9 (with an increase of 31% in the mean AUC of warfarin) [see Warnings and Precautions (5.5), and Drug Interactions (7.1)].

In the screening drug-drug interaction study, co-administration of oritavancin resulted in an increase of 18% in the ratio of 1-methylxanthine + 1 methylurate + 5-acetylamino-6-formylamino-3-methyluracil (1X + 1U + AFMU) to 1,7-dimethylurate (17U) concentrations in the urine after administration of caffeine (CYP1A2 probe substrate), and an increase of 16% in the ratio of AFMU to (1X +1U) concentrations in the urine after administration of caffeine (N-Acetyltransferase- 2 probe substrate). Co-administration of oritavancin did not change the mean systemic exposure of caffeine metabolite (Xanthine oxidase probe substrate).

A study to assess the drug-drug interaction potential of a single 1,200 mg dose of oritavancin on the pharmacokinetics of S-warfarin following a single dose was conducted in 36 healthy subjects. S-warfarin PK was evaluated following a single dose of warfarin 25 mg given alone, or administered at the start, 24, or 72 hours after a single 1,200 mg oritavancin dose. The results showed no effect of oritavancin on S-warfarin Cmax or AUC.

12.4 Microbiology

KIMYRSA is a semi-synthetic, lipoglycopeptide antibacterial drug. KIMYRSA exerts a concentration-dependent bactericidal activity in vitro against S. aureus, S. pyogenes, and E. faecalis.

Mechanism of Action

Oritavancin has three mechanisms of action: (i) inhibition of the transglycosylation (polymerization) step of cell wall biosynthesis by binding to the stem peptide of peptidoglycan precursors; (ii) inhibition of the transpeptidation (crosslinking) step of cell wall biosynthesis by binding to the peptide bridging segments of the cell wall; and (iii) disruption of bacterial membrane integrity, leading to depolarization, permeabilization, and cell death. These multiple mechanisms contribute to the concentration-dependent bactericidal activity of oritavancin.

Resistance

In serial passage studies, resistance to oritavancin was observed in isolates of S. aureus and E. faecalis. Resistance to oritavancin was not observed in clinical studies.

Interaction with Other Antimicrobial Agents

In in vitro studies, oritavancin exhibits synergistic bactericidal activity in combination with gentamicin, moxifloxacin or rifampicin against isolates of methicillin-susceptible S. aureus (MSSA), with gentamicin or linezolid against isolates of heterogeneous vancomycin-intermediate S. aureus (hVISA), VISA, and vancomycin-resistant S. aureus (VRSA), and with rifampin against isolates of VRSA. In vitro studies demonstrated no antagonism between oritavancin and gentamicin, moxifloxacin, linezolid or rifampin.

Antibacterial Activity

Oritavancin has been shown to be active against most isolates of the following microorganisms, both in vitro and in clinical infections [see Indications and Usage (1.1)].

Gram-positive Bacteria

Staphylococcus aureus (including methicillin-resistant isolates)

Streptococcus agalactiae

Streptococcus anginosus group (includes S. anginosus, S. intermedius, and S. constellatus)

Streptococcus dysgalactiae

Streptococcus pyogenes

Enterococcus faecalis (vancomycin-susceptible isolates only)

The following in vitro data are available, but their clinical significance is unknown. At least 90 percent of the following bacteria exhibit an in vitro minimum inhibitory concentration (MIC) less than or equal to the susceptible breakpoint for oritavancin against isolates of a similar organism group. However, the efficacy of oritavancin in treating clinical infections due to these bacteria has not been established in adequate and well-controlled clinical trials.

Gram-positive Bacteria

Enterococcus faecium (vancomycin-susceptible isolates only)

Susceptibility Testing Methods

For specific information regarding susceptibility test interpretive criteria and associated test methods and quality control standards recognized by FDA for this drug, please see: https://www.fda.gov/STIC.

12.6 Immunogenicity

Positive indirect and direct antiglobulin tests (IAT/DAT) have been noted with the administration of KIMYRSA and oritavancin in studies with healthy subjects and patients with ABSSSI. The observed incidence of anti-drug antibodies is highly dependent on the sensitivity and specificity of the assay. Differences in assay methods preclude meaningful comparisons of the incidence of anti-drug antibodies in the studies described below with the incidence of anti-drug antibodies in other studies, including those of KIMYRSA or other oritavancin products.

In a randomized, open-label, multi-center ABSSSI study, positive IAT/DAT were reported in 9.6% (5/52) of subjects who received ORBACTIV, another oritavancin product, and 2% (1/50) of subjects who received KIMYRSA. Oritavancin-dependent red blood cell (RBC) antibodies were detected when tested in the presence of drug for three subjects in the oritavancin group 14 days after dosing.

In a multiple-dose study with oritavancin in healthy volunteers, 90% (9/10) of subjects had a positive IAT 14 days after the second infusion.

In a healthy volunteer study, 66% (22/32) of subjects receiving KIMYRSA had a positive IAT 15 days after receiving dosing and one subject had a positive DAT at 8 days after dosing.

There were no reports of hemolysis in subjects who had positive IAT/DAT in any of the above referenced studies.

An in vitro study further evaluated 403 stored plasma samples from 12 healthy subjects and from 101 patients with ABSSSI from previously conducted clinical studies at multiple timepoints in healthy subjects and in patients with ABSSSI. In samples collected during the 15- and 8-day windows following single-dose treatment in healthy volunteers (Study MDCO-ORI-15-01) and in patients with ABSSSI (Study ML-ORI-201), respectively, low level (<8) direct agglutinating (IgM) anti-oritavancin antibodies were detected in 19 of 113 (17%) subjects. There was no identified clinically significant effect of anti-drug antibodies on pharmacokinetics, pharmacodynamics, safety, or effectiveness of single-dose oritavancin. No hematologic adverse events were reported for subjects with a positive titer.

There were no identified clinically significant effects of anti-drug antibodies on pharmacokinetics, pharmacodynamics, safety, or effectiveness of KIMYRSA over the treatment duration of 14 days.

Positive IAT may interfere with cross-matching before blood transfusion [see Drug Interactions (7.2)].

13 NONCLINICAL TOXICOLOGY

13.1 Carcinogenesis, Mutagenesis, Impairment of Fertility

Long term studies in animals have not been conducted to determine the carcinogenic potential of oritavancin.

No mutagenic or clastogenic potential of oritavancin was found in a battery of tests, including an Ames assay, in vitro chromosome aberration assay in Chinese hamster ovary cells, in vitro forward mutation assay in mouse lymphoma cells and an in vivo mouse micronucleus assay.

Oritavancin did not affect the fertility or reproductive performance of male rats (exposed to daily doses up to 30 mg/kg for at least 4 weeks) and female rats (exposed to daily doses up to 30 mg/kg for at least 2 weeks prior to mating). Those daily doses would be equivalent to a human dose of 300 mg, or 25% of clinical dose. Higher doses were not evaluated in nonclinical fertility studies.

14 CLINICAL STUDIES

14.1 Acute Bacterial Skin and Skin Structure Infections (ABSSSI)

A total of 1987 adults with clinically documented ABSSSI suspected or proven to be due to Gram-positive pathogens were randomized into two identically designed, randomized, double-blind, multi-center, multinational, non-inferiority trials (Trial 1 and Trial 2) comparing a single 1,200 mg intravenous dose of oritavancin to intravenous vancomycin (1 g or 15 mg/kg every 12 hours) for 7 to 10 days. The primary analysis population (modified intent to treat, mITT) included all randomized patients who received any study drug. Patients could receive concomitant aztreonam or metronidazole for suspected Gram-negative and anaerobic infection, respectively. Patient demographic and baseline characteristics were balanced between treatment groups. Approximately 64% of patients were Caucasian and 65% were males. The mean age was 45 years and the mean body mass index was 27 kg/m^2. Across both trials, approximately 60% of patients were enrolled from the United States and 27% of patients from Asia. A history of diabetes was present in 14% of patients. The types of ABSSSI across both trials included cellulitis/erysipelas (40%), wound infection (29%), and major cutaneous abscesses (31%). Median infection area at baseline across both trials was 266.6 cm^2. The primary endpoint in both trials was early clinical response (responder), defined as cessation of spread or reduction in size of baseline lesion, absence of fever, and no rescue antibacterial drug at 48 to 72 hours after initiation of therapy.

Table 4 provides the efficacy results for the primary endpoint in Trial 1 and Trial 2 in the primary analysis population.

Table 4: Clinical Response Rates in ABSSSI Trials using Responders [Cessation of spread or reduction in size of baseline lesion, absence of fever (<37.7°C) and no rescue antibacterial drug at 48 to 72 hours.] , [Patients who died at 48 to 72 hours, after initiation of therapy or who had increase in lesion size at 48 to 72 hours, after initiation of therapy or who used non-study antibacterial therapy during first 72 hours or who had an additional, unplanned, surgical procedure or who had missing measurements during the first 72 hours from initiation of study drug were classified as non-responders.] at 48-72 Hours after Initiation of Therapy
 | Oritavancin n /N (%) | Vancomycin n /N (%) | Difference (95% CI) [95% CI based on the Normal approximation to Binomial distribution.]
Trial 1 | 391/475 (82.3) | 378/479 (78.9) | 3.4 (-1.6, 8.4)
Trial 2 | 403/503 (80.1) | 416/502 (82.9) | -2.7 (-7.5, 2.0)

A key secondary endpoint in these two ABSSSI trials evaluated the percentage of patients achieving a 20% or greater reduction in lesion area from baseline at 48-72 hours after initiation of therapy. Table 5 summarizes the findings for this endpoint in the two ABSSSI trials.

Table 5: Clinical Response Rates [Patients who died at 48 to 72 hours, after initiation of therapy or who had increase in lesion size at 48 to 72 hours, after initiation of therapy or who used non-study antibacterial therapy during first 72 hours or who had an additional, unplanned, surgical procedure or who had missing measurements during the first 72 hours from initiation of study drug were classified as non-responders.] in ABSSSI Trials using Reduction in Lesion Area of 20% or Greater at 48-72 Hours after Initiation of Therapy
 | Oritavancin n /N (%) | Vancomycin n /N (%) | Difference (95% CI) [95% CI based on the Normal approximation to Binomial distribution.]
Trial 1 | 413/475 (86.9) | 397/479 (82.9) | 4.1 (-0.5, 8.6)
Trial 2 | 432/503 (85.9) | 428/502 (85.3) | 0.6 (-3.7, 5.0)

Another secondary efficacy endpoint in the two trials was investigator-assessed clinical success at post therapy evaluation at Day 14 to 24 (7 to 14 days from end of blinded therapy). A patient was categorized as a clinical success if the patient experienced a complete or nearly complete resolution of baseline signs and symptoms related to primary ABSSSI site (erythema, induration/edema, purulent drainage, fluctuance, pain, tenderness, local increase in heat/warmth) such that no further treatment with antibacterial drugs was needed.

Table 6 summarizes the findings for this endpoint in the mITT and clinically evaluable population in these two ABSSSI trials. Note that there are insufficient historical data to establish the magnitude of drug effect for antibacterial drugs compared with placebo at the post therapy visits. Therefore, comparisons of oritavancin to vancomycin based on clinical success rates at these visits cannot be utilized to establish non-inferiority conclusions.

Table 6: Clinical Success Rates [Clinical success was defined if the patient experienced a complete or nearly complete resolution of baseline signs and symptoms as described above.] in ABSSSI Trials at the Follow-Up Visit (7-14 days after end of therapy)
 | Oritavancin n /N (%) | Vancomycin n /N (%) | Difference (95% CI) [95% CI based on the Normal approximation to Binomial distribution.]
Trial 1
mITT [mITT population consisted of all randomized patients who received study drug; CE population consisted of all mITT patients who did not have violations of inclusion and exclusion criteria, completed treatment and had investigator assessment at the Follow-Up Visit.] | 378/475 (79.6) | 383/479 (80.0) | -0.4 (-5.5, 4.7)
CE | 362/394 (91.9) | 370/397 (93.2) | -1.3 (-5.0,2.3)
Trial 2
mITT | 416/503 (82.7) | 404/502 (80.5) | 2.2 (-2.6, 7.0)
CE | 398/427 (93.2) | 387/408 (94.9) | -1.6 (-4.9,1.6)

Outcomes by Baseline Pathogen: Table 7 shows outcomes in patients with an identified baseline pathogen in the microbiological Intent-to-Treat (microITT) population in a pooled analysis of Trial 1 and Trial 2. The outcomes shown in the table are clinical response rates at 48 to 72 hours and clinical success rates at follow-up study day 14 to 24.

Table 7: Outcomes by Baseline Pathogen (microITT)
 | At 48-72 hours |  |  |  | Study day 14 to 24
 | Early Clinical Responder [Early clinical response defined as a composite of the cessation of spread or reduction in size of baseline lesion, absence of fever and no rescue antibacterial drug at 48-72 hours.] |  | ≥ 20% reduction in lesion size [Patients achieving a 20% or greater reduction in lesion area from baseline at 48-72 hours after initiation of therapy.] |  | Clinical Success [Clinical success was defined if the patient experienced a complete or nearly complete resolution of baseline signs and symptoms as described above.]
Pathogen [Baseline bacteremia in the oritavancin arm with relevant microorganisms causing ABSSSI included four subjects with MSSA and seven subjects with MRSA. Eight of these eleven subjects were responders at 48 to 72 hours after initiation of therapy.] | Oritavancin n/N (%) | Vancomycin n/N (%) | Oritavancin n/N (%) | Vancomycin n/N (%) | Oritavancin n/N (%) | Vancomycin n/N (%)
Staphylococcus aureus | 388/472 (82.2) | 395/473 (83.5) | 421/472 (89.2) | 407/473 (86.0) | 390/472 (82.6) | 398/473 (84.1)
Methicillin-susceptible | 222/268 (82.8) | 233/272 (85.7) | 231/268 (86.2) | 232/272 (85.3) | 220/268 (82.1) | 229/272 (84.2)
Methicillin-resistant | 166/204 (81.4) | 162/201 (80.6) | 190/204 (93.1) | 175/201 (87.1) | 170/204 (83.3) | 169/201 (84.1)
Streptococcus pyogenes | 21/31 (67.7) | 23/32 (71.9) | 24/31 (77.4) | 24/32 (75.0) | 25/31 (80.6) | 23/32 (71.9)
Streptococcus agalactiae | 7/8 (87.5) | 12/12 (100.0) | 8/8 (100.0) | 12/12 (100.0) | 7/8 (87.5) | 11/12 (91.7)
Streptococcus dysgalactiae | 7/9 (77.8) | 6/6 (100.0) | 6/9 (66.7) | 5/6 (83.3) | 7/9 (77.8) | 3/6 (50.0)
Streptococcus anginosus group | 28/33 (84.8) | 40/45 (88.9) | 29/33 (87.9) | 42/45 (93.3) | 25/33 (75.8) | 38/45 (84.4)
Enterococcus faecalis | 11/13 (84.6) | 10/12 (83.3) | 10/13 (76.9) | 8/12 (66.7) | 8/13 (61.5) | 9/12 (75.0)

16 HOW SUPPLIED/STORAGE AND HANDLING

16.1 How Supplied/Storage

KIMYRSA is supplied as a sterile white to off-white or pink lyophilized powder in single-dose clear glass vials containing 1,200 mg of oritavancin. One vial is packaged in a carton to supply a single 1,200 mg dose treatment (NDC 70842-225-01).

KIMYRSA vials should be stored at 20ºC to 25ºC (68ºF to 77ºF); excursions permitted to 15ºC to 30ºC (59ºF to 86ºF) [see USP, Controlled Room Temperature (CRT)].

17 PATIENT COUNSELING INFORMATION

Allergic Reactions

Patients should be advised that allergic reactions, including serious allergic reactions, could occur and that serious reactions require immediate treatment. They should inform their healthcare provider about any previous hypersensitivity reactions to oritavancin products, other glycopeptides (vancomycin, telavancin, or dalbavancin) or other allergens.

Diarrhea

Patients should be advised that diarrhea is a common problem caused by antibacterial drugs including KIMYRSA, which usually resolves when the drug is discontinued. Sometimes, frequent watery or bloody diarrhea may occur and may be a sign of a more serious intestinal infection. If severe watery or bloody diarrhea develops, patients should contact their healthcare provider.

Development of Antibacterial Resistance

Patients should be counseled that antibacterial drugs including KIMYRSA should only be used to treat bacterial infections. They do not treat viral infections (e.g. the common cold). When KIMYRSA is prescribed to treat a bacterial infection, patients should be told that although it is common to feel better early in the course of therapy, the medication should be taken exactly as directed. Skipping doses or not completing the full course of therapy may (1) decrease the effectiveness of the immediate treatment and (2) increase the likelihood that bacteria will develop resistance and will not be treatable by KIMYRSA or other antibacterial drugs in the future.

Marketed By:
Melinta Therapeutics, LLC
Parsippany, New Jersey 07054 USA

©2025 Melinta Therapeutics, LLC. All rights reserved.

MEL100-R002

PRINCIPAL DISPLAY PANEL - 1,200 mg Vial Label

Rx only
NDC 70842-225-01

Kimyrsa®
(oritavancin) for injection

1,200 mg per vial

Must be reconstituted and
further diluted to a final
volume of 250 mL

For Intravenous Infusion Only
Single-dose Vial
Discard Unused Portion

PRINCIPAL DISPLAY PANEL - 1,200 mg Vial Carton

Rx only
NDC 70842-225-01

Kimyrsa®
(oritavancin)
for injection

1,200 mg per vial

Must be reconstituted
and further diluted
to a final volume
of 250 mL

For Intravenous Infusion Only
Single-dose Vial
Discard Unused Portion